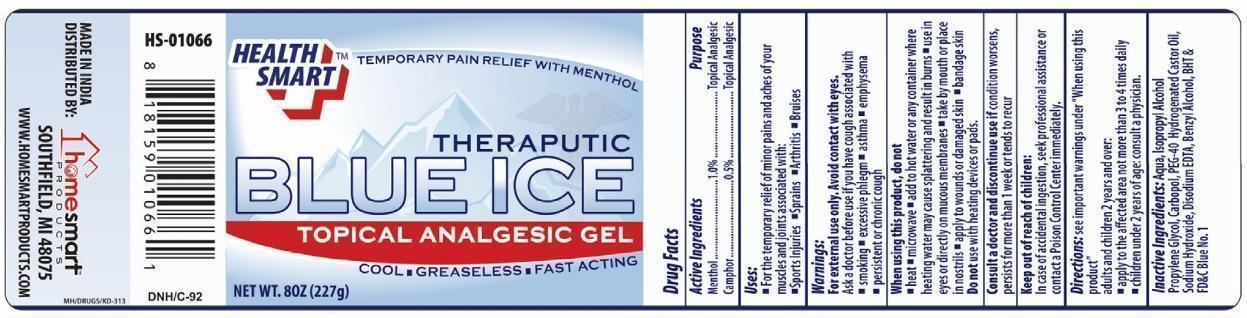 DRUG LABEL: Blue Ice Topical Analgesic Gel
NDC: 52862-901 | Form: GEL
Manufacturer: International Wholesale
Category: otc | Type: HUMAN OTC DRUG LABEL
Date: 20250703

ACTIVE INGREDIENTS: CAMPHOR (SYNTHETIC) 0.5 g/100 g; MENTHOL 1 g/100 g
INACTIVE INGREDIENTS: BENZYL ALCOHOL; EDETATE DISODIUM; BUTYLATED HYDROXYTOLUENE; CARBOMER 940; PROPYLENE GLYCOL; PEG-40 HYDROGENATED CASTOR OIL; FD&C BLUE NO. 1; WATER; SODIUM HYDROXIDE; AMMONIA; ISOPROPYL ALCOHOL

HEALTH SMART BLUE ICE TOPICAL ANALGESIC

Active Ingredient

Menthol 1.0%
Camphor 0.5%

Purpose

Topical Analgesic

Uses:

- for temporary relief of minor aches and pains in muscles and joints associated with:
- simple backaches,
- strains
- sprains
- sports injuries
- arthritis
- bruises

Warnings

FOR EXTERNAL USE ONLY

Do not use:

- with other topical pain relievers
- with heating pads or heating devices

When using this product

- do not use in or near eyes
- do not apply to wounds or damaged skin
- do not bandage tightly

Stop use and ask a doctor if

- condition worsens
- symptoms last more than 7 days or clear up and occur again within a few days
- redness or irritation develops

If pregnant or breastfeeding

ask a health professional before use

KEEP OUT OF REACH OF CHILDREN

If swallowed get Medical Help or contact a Poison Control Center right away

Directions

- clean affected area before applying product
- adults and children 2 years of age and older; apply to affected area not more than 3 to 4 times daily

Inactive Ingredients

ammonium hydroxide, carbomer, cupric sulfate, FD&C Blue No. 1, isopropyl alcohol, magnesium sulfate, sodium hydroxide, thymol, water